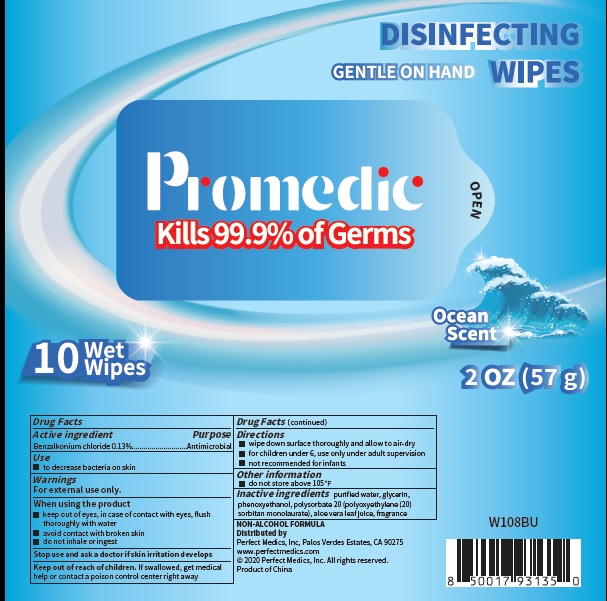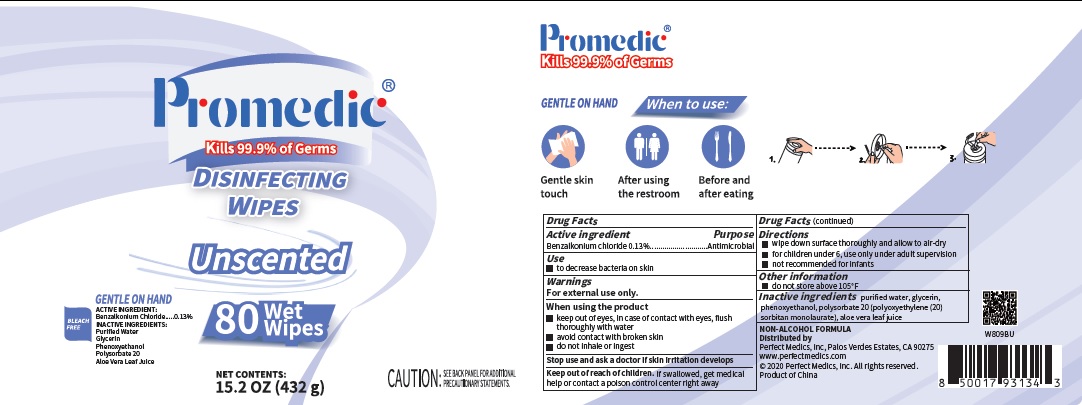 DRUG LABEL: Promedic
NDC: 79134-001 | Form: CLOTH
Manufacturer: Perfect Medics, Inc
Category: otc | Type: HUMAN OTC DRUG LABEL
Date: 20200916

ACTIVE INGREDIENTS: Benzalkonium chloride 0.13 g/100 mL
INACTIVE INGREDIENTS: WATER; GLYCERIN; PHENOXYETHANOL; POLYSORBATE 20; ALOE VERA LEAF; FRAGRANCE LAVENDER & CHIA F-153480

Promedic DISINFECTING WIPES

Active Ingredients

Benzalkonium chloride 0.13%.

Purpose

Antiseptic

Warnings

For external use only.

When using the product

- Keep out of eyes, in case of contact with eyes, flush thoroughly with water
- Avoid contact with broken skin
- Do not inhale or ingest

Stop use and ask a doctor if skin irritation develops.

Uses

- to decrease bacteria on the skin that could cause disease.

Directions

- Wipe down surface thoroughly and allow to air-dry.
- For children under 6, use only under adult supervision.
- Not recommended for infants.

Keep Out of Reach of Children.

- If swallowed, get medical help or contact a poison control center right away.

Other Information

- do not store above 105F.

Inactive Ingredients

Purified water, glycerin, phenoxyethanol, polysorbate 20 (Polyoxyethylene (20) sorbitan monolaurate), aloe vera leaf juice.